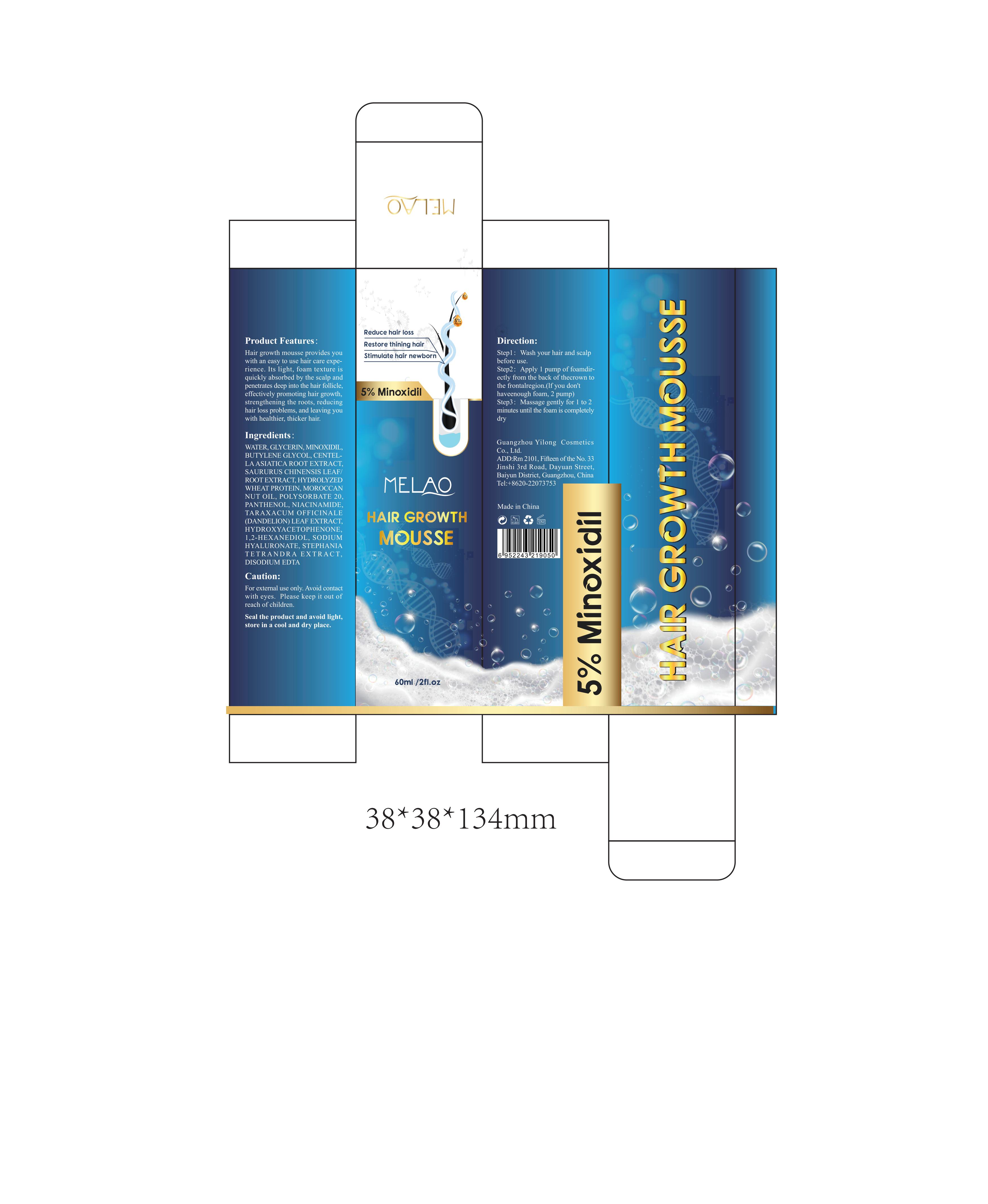 DRUG LABEL: MELAO HAIR GROWTH MOUSSE
NDC: 83566-133 | Form: AEROSOL, FOAM
Manufacturer: Guangdong Aimu Biological Technology Co., Ltd
Category: otc | Type: HUMAN OTC DRUG LABEL
Date: 20250625

ACTIVE INGREDIENTS: GLYCERIN 1 g/100 mL; PANTHENOL 1 g/100 mL; MINOXIDIL 5 g/100 mL
INACTIVE INGREDIENTS: WATER; BUTYLENE GLYCOL; NIACINAMIDE; SAURURUS CHINENSIS FLOWER; CENTELLA ASIATICA ROOT

MELAO HAIR GROWTH MOUSSE

Active ingredients

PANTHENOL 1%
MINOXIDIL 5%
NIACINAMIDE 1%
CENTELLA ASIATICA ROOT EXTRACT 2%
SAURURUS CHINENSIS LEAF/ROOT EXTRACT 2%

Purpose

HAIR GROWTH

Uses

Step1: Wash your hair and scalp before use.
Step2: Apply 1 pump of foamdirectly from the back of thecrown to the frontalregion.(lf you don't haveenough foam, 2 pump).
Step3: Massage gently for 1 to 2 minutes until the foam is completely dry.

Warnings

For external use only.

Stop use

Stop use and ask a doctor if rash occurs.

Do not use

on damaged or broken skin.

When using this product

keep out of eyes. Rinse withwater to remove.

Keep out of reach of children.

If swallowed, get medical help or contact a Poison Control Center right away.

DOSAGE AND ADMINISTRATION

Squeezeout an appropriate amount of hair growth mousse and spread on the scalp

INACTIVE INGREDIENT

WATER
GLYCERIN
BUTYLENE GLYCOL
TARAXACUM OFFICINALE (DANDELION) LEAF EXTRACT
STEPHANIA TETRANDRA EXTRACT
HYDROLYZED WHEAT PROTEIN
MOROCCAN NUT OIL
POLYSORBATE 20
SODIUM HYALURONATE
HYDROXYACETOPHENONE
1,2-HEXANEDIOL
DISODIUM EDTA
PEG-40 HYDROGENATED CASTOR OL
AROMA